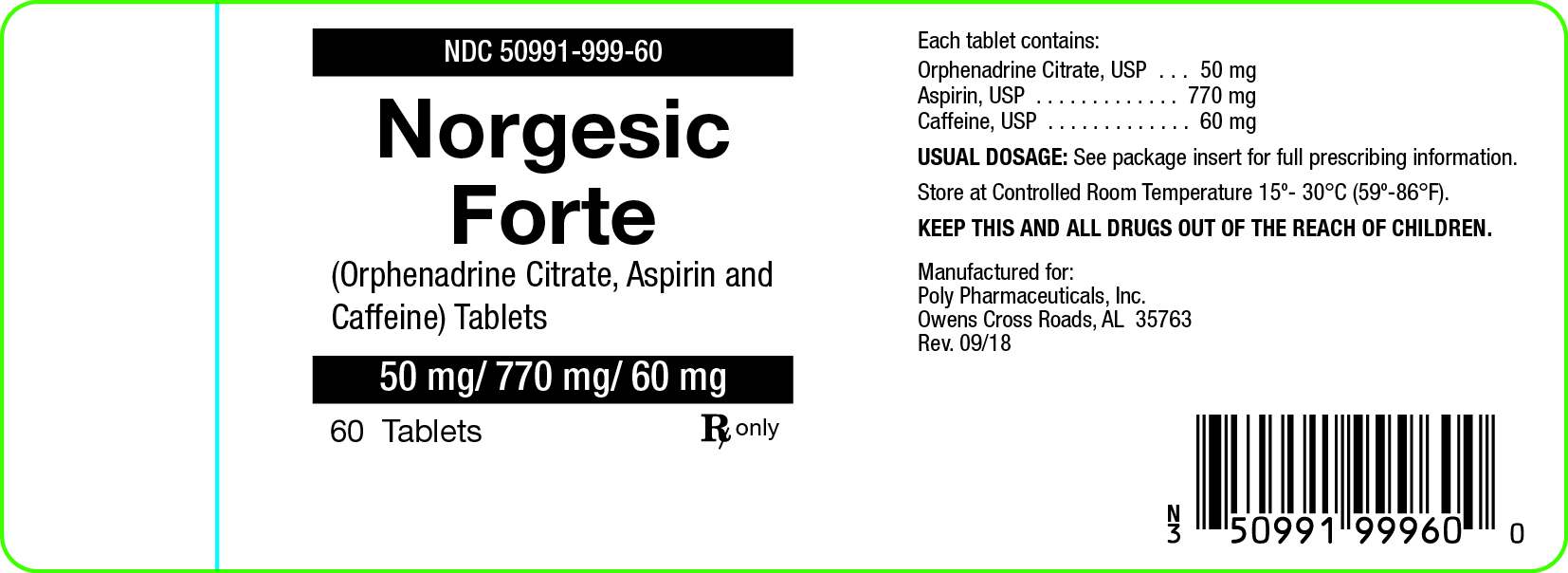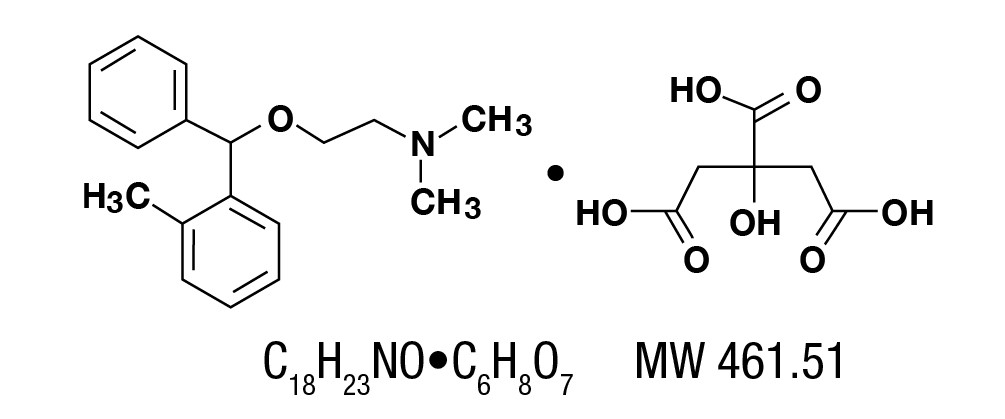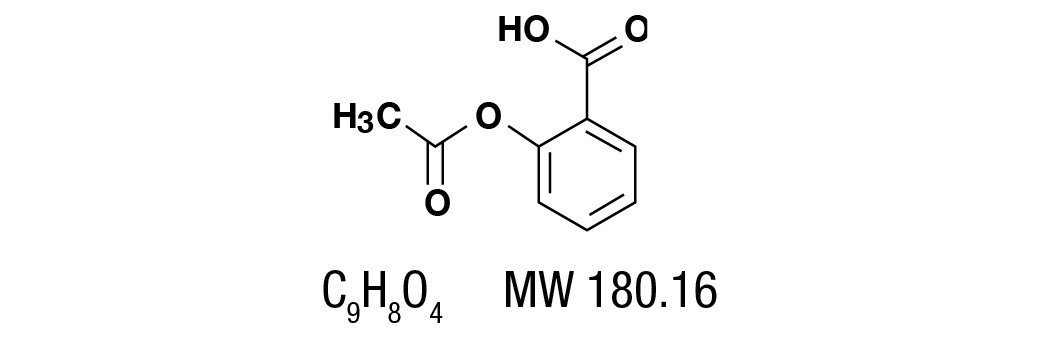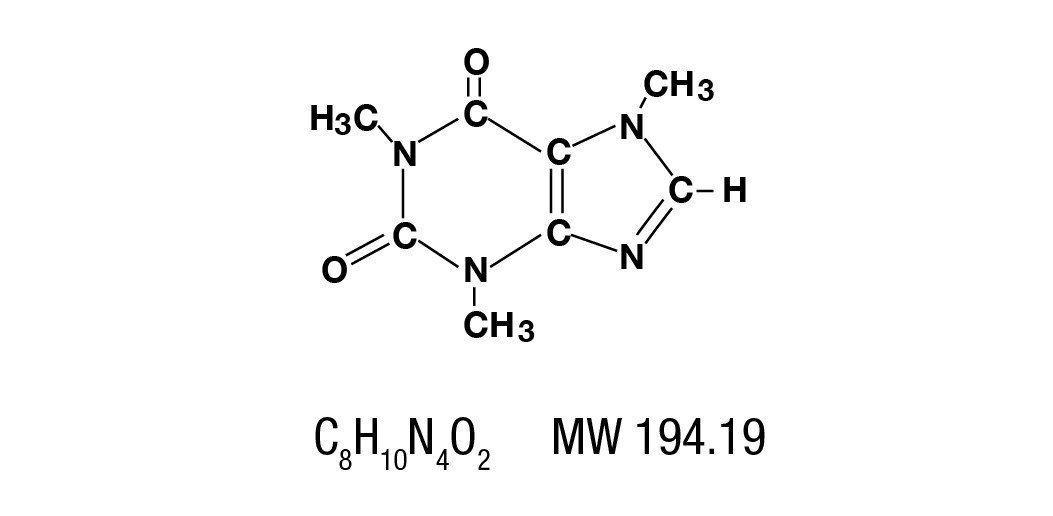 DRUG LABEL: Norgesic Forte
NDC: 50991-999 | Form: TABLET, MULTILAYER
Manufacturer: Poly Pharmaceuticals, Inc.
Category: prescription | Type: HUMAN PRESCRIPTION DRUG LABEL
Date: 20251230

ACTIVE INGREDIENTS: ORPHENADRINE CITRATE 50 mg/1 1; ASPIRIN 770 mg/1 1; CAFFEINE 60 mg/1 1
INACTIVE INGREDIENTS: CROSCARMELLOSE SODIUM; FD&C BLUE NO. 1; D&C YELLOW NO. 10; CELLULOSE, MICROCRYSTALLINE; POVIDONE; SILICON DIOXIDE; SODIUM LAURYL SULFATE; STARCH, CORN; STEARIC ACID; ANHYDROUS LACTOSE

Norgesic Forte

DESCRIPTION

Each Norgesic Forte tablet, for oral administration, contains Orphenadrine Citrate 50 mg, Aspirin 770 mg, Caffeine 60 mg.

In addition, each tablet contains the following inactive ingredients, anhydrous lactous, colloidal silicon dioxide, D&C yellow #10, FD&C blue #1, zinc stearate, providone, pregetanized starch, and stearic acid.

Orphenadrine citrate, (2-dimethylaminoethyl 2-methybenzhydryl ether citrate). It is as a white, practically odorless, crystalline powder, having a bitter taste. It is sparingly soluble in water, slightly soluble in alcohol. It has the following structural formula:

Aspirin, salicylic acid acetate, is a non-opiate analgesic, anti-inflammatory and antipyretic agent. It occurs as a white, crystalline tabular or needle like powder and is odorless or has a faint odor. It is sparingly soluble in water, freely soluble in alcohol and chloroform. It has the following structural formula:

Caffeine is a central nervous system stimulant which occurs as a white powder or white glistening needles, usually matted together. It is sparingly soluble in alcohol, and freely soluble in chloroform. The chemical name for caffeine is 1,3,7-Trimethylxanthine. It has the following structural formula:

CLINICAL PHARMACOLOGY

Orphenadrine citrate is a centrally acting (brain stem) compound which in animals selectively blocks facilitatory functions of the reticular formulation. Orphenadrine does not produce myoneural block, nor does it affect crossed extensor reflexes. Orphenadrine prevents nicotine-induced convulsions but not those produced by strychnine.

Chronic administration of Orphenadrine Citrate, Aspirin, and Caffeine to dogs and rats has revealed no drug-related toxicity. No blood or urine changes were observed, nor were there any macroscopic or microscopic pathological changes detected. Extensive experience with combinations containing aspirin and caffeine has established them as safe agents. The addition of orphenadrine citrate does not alter the toxicity of aspirin and caffeine.

The mode of therapeutic action of orphenadrine has not been clearly identified, but may be related to its analgesic properties. Orphenadrine citrate also possesses anticholinergic actions.

INDICATIONS AND USAGE

Norgesic Forte 50 mg/770mg/60 mg Tablets are indicated in:

1. Symptomatic relief of mild to moderate pain of acute musculoskeletal disorders.
2. The orphenadrine component is indicated as an adjunct to rest, physical therapy, and other measures for the relief of discomfort associated with acute painful musculoskeletal conditions.
  The mode of action of orphenadrine has not been clearly identified, but may be related to its analgesic properties. Norgesic Forte Tablets do not directly relax tense skeletal muscles in man.

CONTRAINDICATIONS

Because of the mild anti-cholinergic effect of orphenadrine, Norgesic Forte Tablets should not be used in patients with glaucoma, pyloric or duodenal obstruction, achalasia, prostatic hypertrophy, or obstructions at the bladder neck. Norgesic Forte Tablets are also contraindicated in patients with myasthenia gravis and in patients known to be sensitive to aspirin or caffeine.

The drug is contraindicated in patients who have demonstrated a previous hypersensitivity to the drug.

WARNINGS

Reye’s Syndrome may develop in individuals who have chicken pox, influenza, or flu symptoms. Some studies suggest possible association between the development of Reye’s Syndrome and the use of medicines containing salicylate or aspirin. Norgesic Forte Tablets 50mg/770mg/60mg contain aspirin and therefore are not recommended for use in patients with chicken pox, influenza, or flu symptoms.

Norgesic Forte Tablets may impair the ability of the patient to engage in potentially hazardous activities such as operating machinery or driving a motor vehicle: ambulatory patients should therefore be cautioned accordingly.

Aspirin should be used with extreme caution in the presence of peptic ulcers and coagulation abnormalities.

Usage in Pregnancy

Risk Summary

Use of NSAIDs, including aspirin, can cause premature closure of the fetal ductus arteriosus and
fetal renal dysfunction leading to oligohydramnios and, in some cases, neonatal renal

impairment. Because of these risks, limit dose and duration of Orphengesic Forte Tablets use
between about 20 and 30 weeks of gestation, and avoid Orphengesic Forte Tablets use at about
30 weeks of gestation and later in pregnancy [see WARNINGS; Fetal Toxicity].
Premature Closure of Fetal Ductus Arteriosus
Use of NSAIDs, including aspirin, at about 30 weeks gestation or later in pregnancy
increases the risk of premature closure of the fetal ductus arteriosus.
Oligohydramnios/Neonatal Renal Impairment
Use of NSAIDs at about 20 weeks gestation or later in pregnancy has been associated with
cases of fetal renal dysfunction leading to oligohydramnios, and in some cases, neonatal
renal impairment.
Data from observational studies regarding other potential embryofetal risks of NSAID use in
women in the first or second trimesters of pregnancy are inconclusive.

Based on animal data, prostaglandins have been shown to have an important role in endometrial
vascular permeability, blastocyst implantation, and decidualization. In animal studies,
administration of prostaglandin synthesis inhibitors such as aspirin, resulted in increased pre- and
post-implantation loss. Prostaglandins also have been shown to have an important role in fetal
kidney development. In published animal studies, prostaglandin synthesis inhibitors have been
reported to impair kidney development when administered at clinically relevant doses.

The estimated background risk of major birth defects and miscarriage for the indicated
population(s) is unknown. All pregnancies have a background risk of birth defect, loss, or other
adverse outcomes. In the U.S. general population, the estimated background risk of major birth
defects and miscarriage in clinically recognized pregnancies is 2-4% and 15-20%, respectively.

Clinical Considerations
Fetal/Neonatal Adverse Reactions
Premature Closure of Fetal Ductus Arteriosus: Avoid use of NSAIDs in women at about 30
weeks gestation and later in pregnancy, because NSAIDs, including Orphengesic Forte Tablets,
can cause premature closure of the fetal ductus arteriosus (see WARNINGS; Fetal Toxicity).
Oligohydramnios/Neonatal Renal Impairment
If an NSAID is necessary at about 20 weeks gestation or later in pregnancy, limit the use to the
lowest effective dose and shortest duration possible. If Orphengesic Forte Tablets treatment
extends beyond 48 hours, consider monitoring with ultrasound for oligohydramnios. If
oligohydramnios occurs, discontinue Orphengesic Forte Tablets and follow up according to
clinical practice (see WARNINGS; Fetal Toxicity).

Data
Human Data
Premature Closure of Fetal Ductus Arteriosus :
Published literature reports that the use of NSAIDs at about 30 weeks of gestation and later in
pregnancy may cause premature closure of the fetal ductus arteriosus.

Oligohydramnios/Neonatal Renal Impairment:

Published studies and postmarketing reports describe maternal NSAID use at about 20 weeks
gestation or later in pregnancy associated with fetal renal dysfunction leading to
oligohydramnios, and in some cases, neonatal renal impairment. These adverse outcomes are
seen, on average, after days to weeks of treatment, although oligohydramnios has been
infrequently reported as soon as 48 hours after NSAID initiation. In many cases, but not all, the
decrease in amniotic fluid was transient and reversible with cessation of the drug. There have
been a limited number of case reports of maternal NSAID use and neonatal renal dysfunction
without oligohydramnios, some of which were irreversible. Some cases of neonatal renal
dysfunction required treatment with invasive procedures, such as exchange transfusion or
dialysis.

Methodological limitations of these postmarketing studies and reports include lack of a control
group; limited information regarding dose, duration, and timing of drug exposure; and
concomitant use of other medications. These limitations preclude establishing a reliable estimate
of the risk of adverse fetal and neonatal outcomes with maternal NSAID use. Because the
published safety data on neonatal outcomes involved mostly preterm infants, the generalizability
of certain reported risks to the full-term infant exposed to NSAIDs through maternal use is
uncertain.

Usage in Children

The safe and effective use of this drug in children has not been established. Usage of this drug in children under 12 years of age is not recommended.

Fetal Toxicity
Premature Closure of Fetal Ductus Arteriosus:
Avoid use of NSAIDs, including Norgesic Forte Tablets, in pregnant women at about 30
weeks gestation and later. NSAIDs including Orphengesic Forte Tablets, increase the risk of
premature closure of the fetal ductus arteriosus at approximately this gestational age.
Oligohydramnios/Neonatal Renal Impairment:

Use of NSAIDs, including Norgesic Forte Tablets, at about 20 weeks gestation or later in
pregnancy may cause fetal renal dysfunction leading to oligohydramnios and, in some cases,
neonatal renal impairment. These adverse outcomes are seen, on average, after days to weeks of
treatment, although oligohydramnios has been infrequently reported as soon as 48 hours after
NSAID initiation. Oligohydramnios is often, but not always, reversible with treatment
discontinuation. Complications of prolonged oligohydramnios may, for example, include limb
contractures and delayed lung maturation. In some postmarketing cases of impaired neonatal
renal function, invasive procedures such as exchange transfusion or dialysis were required.
If NSAID treatment is necessary between about 20 weeks and 30 weeks gestation, limit
Orphengesic Forte Tablets use to the lowest effective dose and shortest duration possible.
Consider ultrasound monitoring of amniotic fluid if Norgesic Forte Tablets treatment extends
beyond 48 hours. Discontinue if oligohydramnios occurs and follow
up according to clinical practice [see PRECAUTIONS; Pregnancy].

Drug Reaction with Eosinophilia and Systemic Symptoms (DRESS)

Drug Reaction with Eosinophilia and Systemic Symptoms (DRESS) has been reported in
patients taking NSAIDs such as Orphengesic Forte Tablets. Some of these events have been fatal
or life-threatening. DRESS typically, although not exclusively, presents with fever, rash,
lymphadenopathy, and/or facial swelling. Other clinical manifestations may include hepatitis,
nephritis, hematological abnormalities, myocarditis, or myositis. Sometimes symptoms of
DRESS may resemble an acute viral infection. Eosinophilia is often present. Because this
disorder is variable in its presentation, other organ systems not noted here may be involved. It is
important to note that early manifestations of hypersensitivity, such as fever or
lymphadenopathy, may be present even though rash is not evident. If such signs or symptoms are
present, discontinue and evaluate the patient immediately.

PRECAUTIONS

Confusion, anxiety and tremors have been reported in a few patients receiving propoxyphene and
orphenadrine concomitantly. As these symptoms may be simply due to an additive effect,
reduction of dosage and/or discontinuation of one or both agents is recommended in such cases.

Safety of continuous long term therapy with Norgesic Forte Tablets has not been established;
therefore, if Norgesic Forte Tablets are prescribed for prolonged use, periodic monitoring of

blood, urine and liver function values is recommended.

Pregnancy
Embryo-Fetal Toxicity
Inform pregnant women to avoid use of aspirin and other NSAIDs starting at 30 weeks gestation
because of the risk of the premature closing of the fetal ductus arteriosus. If treatment with
Norgesic Forte Tablets is needed for a pregnant woman between about 20 to 30 weeks
gestation, advise her that she may need to be monitored for oligohydramnios, if treatment
continues for longer than 48 hours [see WARNINGS; Fetal Toxicity, PRECAUTIONS;
Pregnancy].

Serious Skin Reactions, including DRESS
Advise patients to stop taking Orphengesic Forte Tablets immediately if they develop any type of
rash or fever and to contact their healthcare provider as soon as possible [see Warnings].

ADVERSE REACTIONS

Side effects of Norgesic Forte Tablets are those seen with aspirin and caffeine or those usually associated with mild anticholinergic agents. These may include tachycardia, palpitation, urinary hesitancy or retention, dry mouth, blurred vision, dilation of the pupil, increased intraocular tension, weakness, nausea, vomiting, headache, dizziness, constipation, drowsiness, and rarely, urticaria and other dermatoses. Infrequently, an elderly patient may experience some degree of confusion. Mild central excitation and occasional hallucinations may be observed. These mild side effects can usually be eliminated by reduction in dosage. One case of aplastic anemia associated with the use of Orphenadrine Citrate, Aspirin, and Caffeine Tablets has been reported. No causal relationship has been established. Rare G.I. hemorrhage due to aspirin content may be associated with the administration of Norgesic Forte Tablets. Some patients may experience transient episodes of lightheadedness, dizziness or syncope.

DOSAGE AND ADMINISTRATION

Norgesic Forte Tablets: Adults 1/2 to 1 tablet 3 to 4 times daily.

HOW SUPPLIED

Norgesic Forte Tablets (Orphenadrine Citrate 50mg, Aspirin 770mg, and Caffeine 60mg) Two-layered, white/green capsule shaped, bisected tablets debossed "GA" and "473" with bisect on the white side and plain on the green side are available in bottles of 60 tablets (NDC 50991-999-60).

Store below 30°C (86°F)

Rx Only

Storage

Store at 20°-25°C (68°-77° F) (see USP Controlled Room Temperature).

Protect from moisture.

Manufactured for:

Poly Pharmaceuticals, Inc.

Owens Cross Roads, AL 35763

Rev. 04/21

Norgesic Forte Tablet Label

Norgesic Forte Tablets

50 mg/770 mg/60 mg

Rx only